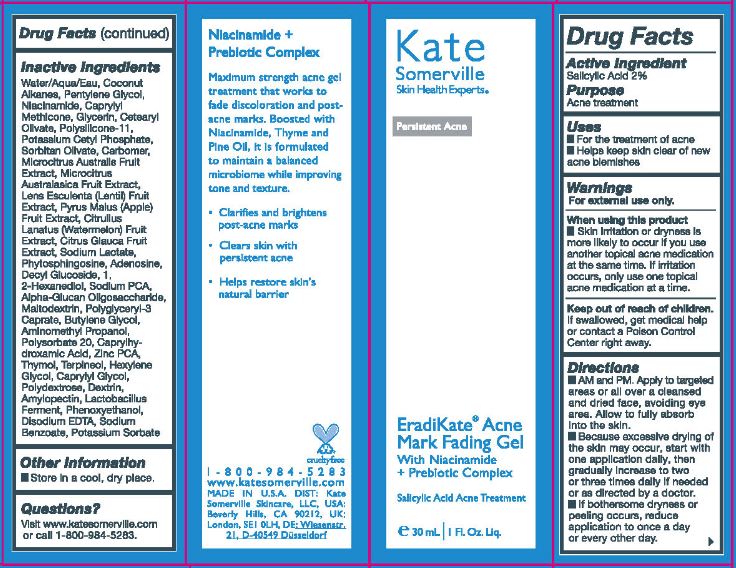 DRUG LABEL: ERADIKATE ACNE MARK FADING
NDC: 72204-903 | Form: GEL
Manufacturer: Rare Beauty Brands Inc.
Category: otc | Type: HUMAN OTC DRUG LABEL
Date: 20251201

ACTIVE INGREDIENTS: SALICYLIC ACID 2 g/100 mL
INACTIVE INGREDIENTS: WATER; COCONUT ALKANES; PENTYLENE GLYCOL; NIACINAMIDE; CAPRYLYL TRISILOXANE; GLYCERIN; CETEARYL OLIVATE; DIMETHICONE/VINYL DIMETHICONE CROSSPOLYMER (SOFT PARTICLE); POTASSIUM CETYL PHOSPHATE; SORBITAN OLIVATE; CARBOMER HOMOPOLYMER, UNSPECIFIED TYPE; MICROCITRUS AUSTRALIS FRUIT; LENTIL; APPLE; WATERMELON; EREMOCITRUS GLAUCA FRUIT; SODIUM LACTATE; PHYTOSPHINGOSINE; ADENOSINE; DECYL GLUCOSIDE; 1,2-HEXANEDIOL; SODIUM PYRROLIDONE CARBOXYLATE; .ALPHA.-GLUCAN OLIGOSACCHARIDE; MALTODEXTRIN; POLYGLYCERYL-3 CAPRATE; BUTYLENE GLYCOL; AMINOMETHYLPROPANOL; POLYSORBATE 20; CAPRYLHYDROXAMIC ACID; ZINC PIDOLATE; THYMOL; TERPINEOL; HEXYLENE GLYCOL; CAPRYLYL GLYCOL; POLYDEXTROSE; ICODEXTRIN; AMYLOPECTIN, UNSPECIFIED SOURCE; LACTOBACILLUS REUTERI; PHENOXYETHANOL; EDETATE DISODIUM; SODIUM BENZOATE; POTASSIUM SORBATE

KATE SOMERVILLE (as PLD) - ERADIKATE ACNE MARK FADING GEL (43479-112)

ACTIVE INGREDIENTS

SALICYLIC ACID- 2%

PURPOSE

ACNE TREATMENT

USES

- FOR THE TREATMENT OF ACNE
- HELPS KEEP SKIN CLEAR OF NEW ACNE BLEMISHES

WARNINGS

FOR EXTERNAL USE ONLY

WHEN USING THIS PRODUCT

- SKIN IRRITATION OR DRYNESS IS MORE LIKELY TO OCCUR IF YOU USE ANOTHER TOPICAL ACNE MEDICATIONAT THE SAME TIME. IF IRRITATION OCCURS, ONLY USE ONE TOPICAL ACNE MEDICATION AT A TIME.

KEEP OUT OF REACH OF CHILDREN. IF SWALLOWED, GET MEDICAL HELP OR CONTACT A POISON CONTROL CENTER RIGHT AWAY.

DIRECTIONS

- AM AND PM. APPLY TO TARGETED AREAS OR ALL OVER A CLEANSED AND DRIED FACE, AVOIDING EYE AREA. ALLOW TO FULLY ABSORB INTO THE SKIN.
- BECAUSE EXCESSIVE DRYING OF THE SKIN MAKE OCCUR, START WITH ONE APPLICATION DAILY, THEN GRADUALLY INCREASE TO TWO OR THREE TIMES DAILY IF NEEDED OR AS DIRECTED BY A DOCTOR.
- IF BOTHERSOME DRYNESS OR PEELING OCCURS, REDUCE APPLICATION TO ONCE A DAY OR EVERY OTHER DAY.

INACTIVE INGREDIENTS

WATER/AQUA/EAU, COCONUT ALKANES, PENTYLENE GLYCOL, NIACINAMIDE, CAPRYLYL METHICONE, GLYCERIN, CETEARYL OLIVATE, POLYSILICONE-11, POTASSIUM CETYL PHOSPHATE, SORBITAN OLIVATE, CARBOMER, MICROCITRUS AUSTRALIS FRUIT EXTRACT, LENS ESCULENTA (LENTIL) FRUIT EXTRACT, PYRUS MALUS (APPLE) FRUIT EXTRACT, CITRULLUS lANATUS (wATERMELON) FRUIT EXTRACT, CITRUS GLAUCA FRUIT EXTRACT, SODIUM LACTATE, PHYTOSPHINGOSINE, ADENOSINE, DECYL GLUCOSIDE, 1,2-HEXANEDIOL, SODIUM PCA, ALPHA-GLUCAN OLIGOSACCHARIDE, MALTODEXTRIN, POLYGLYCERYL-3 CAPRATE, BUTYLENE GLYCOL, AMINOMETHYL PROPANOL, POLYSORBATE 20, CAPRYLHYDROXAMIC ACID, ZINC PCA, THYMOL, TERPINEOL, HEXYLENE GLYCOL, CAPRYLYL GLYCOL, POLYDEXTROSE, DEXTRIN, AMYLOPECTIN, LACTOBACILLUS FERMENT, PHENOXYETHANOL, DISODIUM EDTA, SODIUM BENZOATE, POTASSIUM SORBATE

OTHER INFORMATION

- STORE IN A COOL, DRY PLACE.

QUESTIONS?

VISIT WWW.KATESOMERVILLE.COM OR CALL 1-800-984-5283.